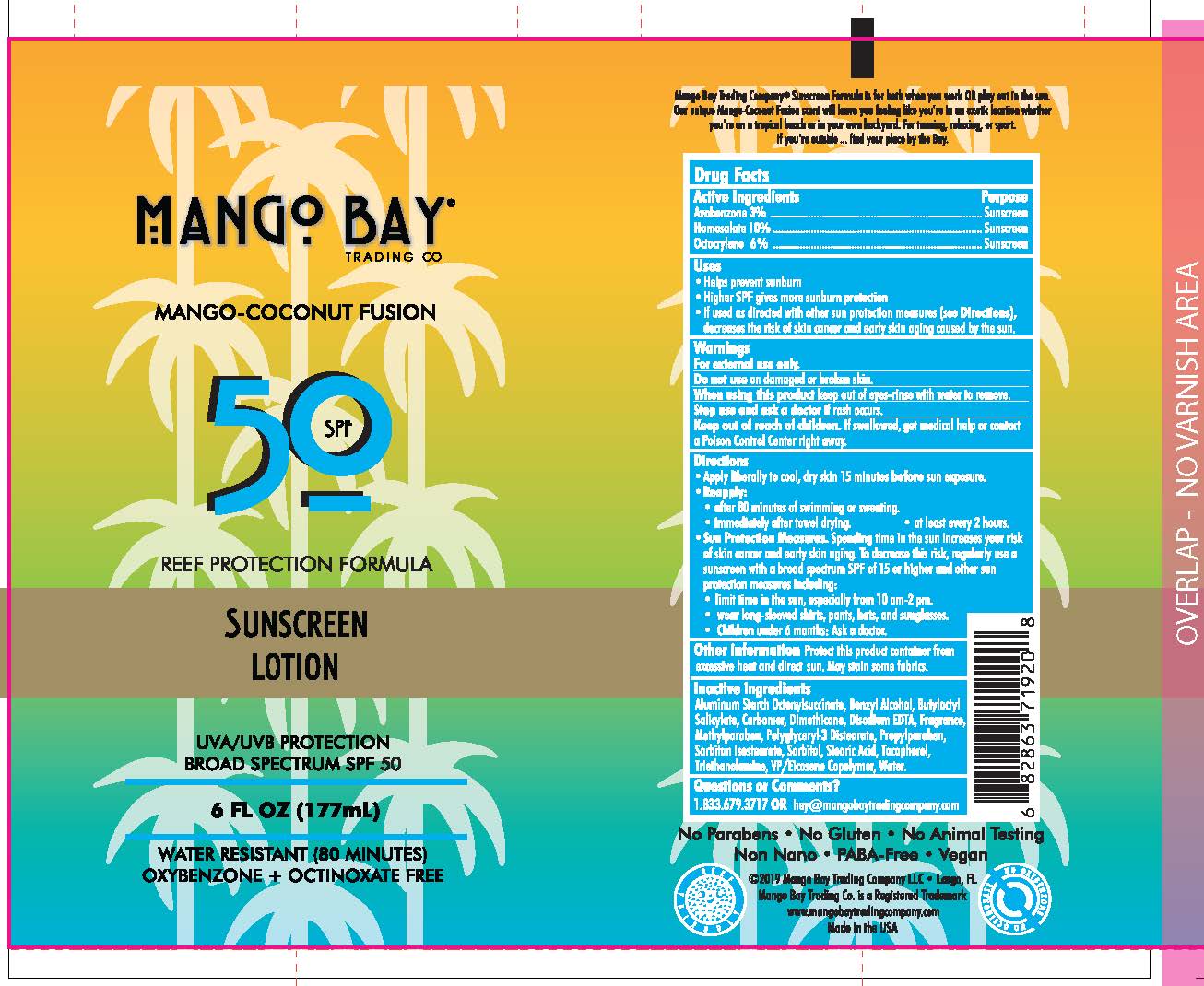 DRUG LABEL: Mango Bay SPF 50
NDC: 72667-035 | Form: LOTION
Manufacturer: Inspec Solutions LLC.
Category: otc | Type: HUMAN OTC DRUG LABEL
Date: 20250506

ACTIVE INGREDIENTS: HOMOSALATE 10 g/100 mL; OCTOCRYLENE 6 g/100 mL; AVOBENZONE 3 g/100 mL
INACTIVE INGREDIENTS: TOCOPHEROL; MAGNESIUM DISODIUM EDTA; WATER; BUTYLOCTYL SALICYLATE; CARBOMER HOMOPOLYMER, UNSPECIFIED TYPE; POLYGLYCERYL-3 DISTEARATE; DIMETHICONE; FRAGRANCE 13576; METHYLPARABEN; PROPYLPARABEN; SORBITAN ISOSTEARATE; SORBITOL; STEARIC ACID; TROLAMINE; VINYLPYRROLIDONE/EICOSENE COPOLYMER; BENZYL ALCOHOL; ALUMINUM STARCH OCTENYLSUCCINATE

Mango Bay SPF 50 Sunscreen Lotion

Active ingredients

Avobenzone 3.0%

Homosalate 15.0%

Octisalate 5.0%

Octocrylene 10.0%

Uses

• Helps prevent sunburn, higher SPF gives more sunburn protection

• retains SPF after XX minutes of activity in the water or sweating

• provides moderate protection against sunburn

• if used as directed with other sun protection measures (see Directions),

Decreases the risk of skin cancer and early skin aging caused by the sun

WARNINGS

For external use only.

Highly Flammable: Do not apply or use product near heat, flame, or while smoking.

When using this product:

• keep out of eyes. Rinse with water to remove.

• Keep away from face to avoid breathing it.

• Do not puncture or incinerate, Contents under pressure

• Do not store at temperature above 120⁰F

Stop use and ask a doctor if rash occurs.

Keep out of reach of children. If swallowed, get medical help or contact a Poison Control Center right away

When using this product:

• keep out of eyes. Rinse with water to remove.

• Keep away from face to avoid breathing it.

• Do not puncture or incinerate, Contents under pressure

• Do not store at temperature above 120⁰F

Stop use and ask a doctor if rash occurs.

Keep out of reach of children. If swallowed, get medical help or contact a Poison Control Center right away

INACTIVE INGREDIENT

Behenyl Alcohol

BHT

Butyloctyl Salocylate

Caprylyl Methicone

Dimethicone

Dimethyl Capramide

Disodium EDTA

Ethylhexyl Stearate

Ethylhexylglycerin

Glyceryl Stearate

Hydrated Silicia

PEG-100 Stearate

Phenoxyethanol

Polyester-8

Sodium Polyacrylate

Styrene/ Acrylate Copolymer

Trideceth-6

Trimethylsiloxysilicate

VP/Hexadecene Copolyer

Water

Xanthan Gum

DIRECTIONS

• Apply liberally 15 minutes before sun exposure.

• Reapply:

after 80 minutes of swimming or sweating
immediately after towel drying
at least every 2 hours

٠Hold container 4 to 6 inches from the skin to apply.
٠Do not spray directly into face. Spray on hands then apply to face.
٠Do not apply in windy conditions.
٠Use in a well-ventilated area.
٠For sunscreen use
٠apply to all areas of the skin exposed to the sun.
٠Reapply as needed or after towel drying, swimming, or sweating.

PURPOSE

Sunscreen

INDICATIONS AND USAGE

- Helps prevent sunburn
- Higher SPF gives more sunburn protection
- If used as directed with other sun protection measures (see DIRECTIONS), decreases the risk of skin cancer and early skin aging caused by the sun.

Do not use on damaged or broken skin.

Stop use and ask a doctor is rash occurs.

OTHER SAFETY INFORMATION

Protect this product container from excessive heat and direct sun. May stain some fabrics.

Questions or Comments?

1.833.679.3717 OR hey@mangobaytradingcompany.com